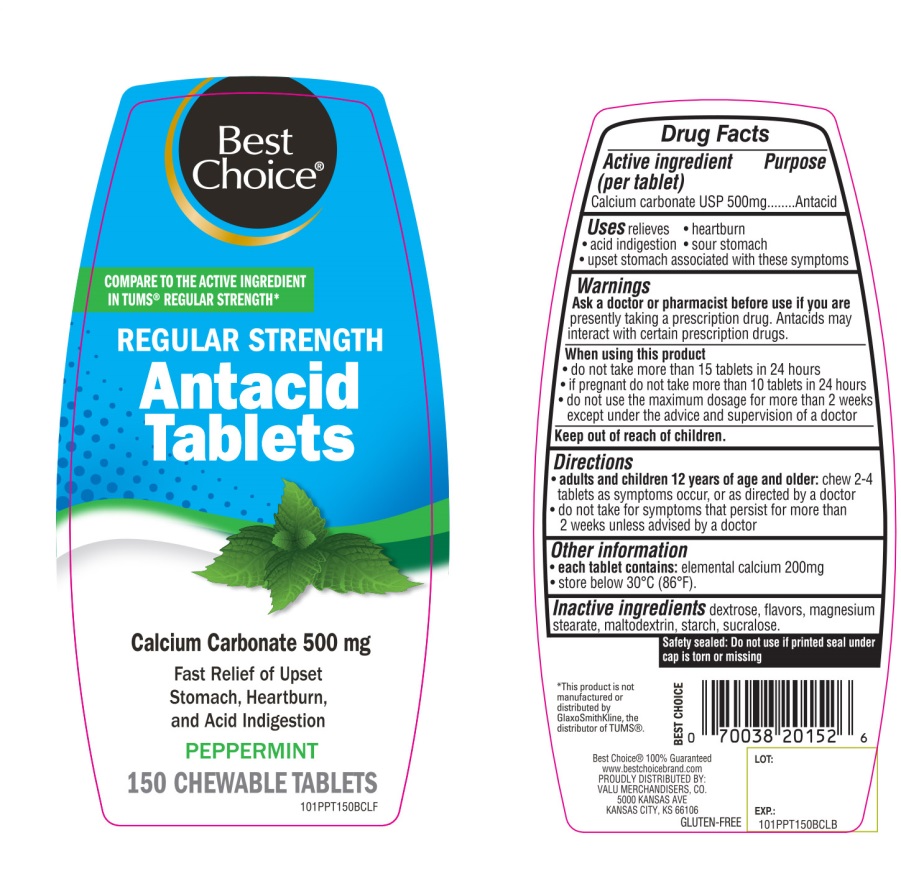 DRUG LABEL: Best Choice

NDC: 63941-101 | Form: TABLET, CHEWABLE
Manufacturer: BEST CHOICE (VALU MERCHANDISERS COMPANY)
Category: otc | Type: HUMAN OTC DRUG LABEL
Date: 20250715

ACTIVE INGREDIENTS: CALCIUM CARBONATE 500 mg/1 1
INACTIVE INGREDIENTS: DEXTROSE, UNSPECIFIED FORM; MAGNESIUM STEARATE; MALTODEXTRIN; STARCH, CORN; SUCRALOSE

Best Choice Regular Strength Antacid Calcium Carbonate Chewable Tablets 150 Count

Active ingredient (per tablet)

Calcium Carbonate USP 500mg

Purpose

Antacid

Uses

relieves

- heartburn
- acid indigestion
- sour stomach
- upset stomach associated with these symptoms

Warnings

Ask a doctor or pharmacist before use if you arepresently taking a prescription drug. Antacids may interact with certain prescription drugs.

When using this product

- do not take more than 15 tablets in 24 hours
- if pregnant do not take more than 10 tablets in 24 hours
- do not use the maximum dosage for more than 2 weeks except under the advice and supervision of a doctor.

Directions

- adults and children 12 years of age and older:chew 2-4 tablets as symptoms occur, or as directed by a doctor
- do not take for symptoms that persist for more than 2 weeks unless advised by a doctor

Other information

- each tablet contains:elemental calcium 200mg
- store below 30°C (86°F)

SAFETY SEALED: DO NOT USE IF PRINTED SEAL UNDER CAP IS TORN OR MISSING

Inactive ingredients

dextrose, flavors, magnesium stearate, maltodextrin, starch, sucralose.

Package/Label Principal Display Panel

NDC 63941-101-50

COMPARE TO THE ACTIVE INGREDIENT IN TUM® REGULAR STRENGTH*

Best Choice®

REGULAR STRENGTH

Antacid Tablets

Calcium Carbonate 500mg

Fast Relief of Upset Stomach, Heartburn and Acid indigestion

PEPPERMINT

150 CHEWABLE TABLETS

K PAREVE

Gluten-Free

Best Choice 100% Guaranteed www.bestchoicebrand.com

PROUDLY DISTRIBUTED BY:

VALU MERCHANDISERS, CO.

5000 KANSAS AVE

KANSAS CITY, KS 66106

*This product is not manufactured or distributed by GlaxoSmithKline LLC, the distributor of TUMS®.